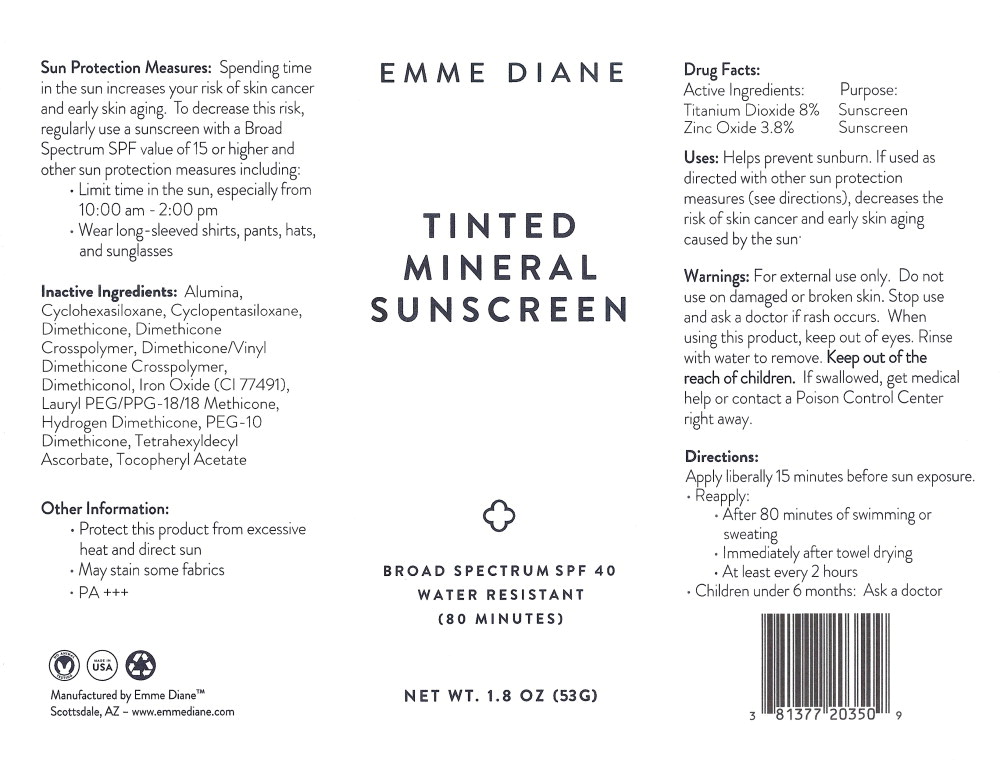 DRUG LABEL: Emme Diane Tinted Mineral Sunscreen
NDC: 81377-203 | Form: CREAM
Manufacturer: Emme Diane, Inc
Category: otc | Type: HUMAN OTC DRUG LABEL
Date: 20250116

ACTIVE INGREDIENTS: Titanium Dioxide 80 mg/1 g; Zinc Oxide 38 mg/1 g
INACTIVE INGREDIENTS: Aluminum Hydroxide; Cyclomethicone 6; Cyclomethicone 5; Dimethicone 20; Dimethicone Crosspolymer (450000 MPA.S AT 12% in Cyclopentasiloxane); Dimethicone/Vinyl Dimethicone Crosspolymer (Soft Particle); Dimethiconol (2000 CST); Brown Iron Oxide; Lauryl PEG/PPG-18/18 Methicone; Hydrogen Dimethicone (20 CST); PEG-10 Dimethicone (600 CST); Tetrahexyldecyl Ascorbate; .Alpha.-Tocopherol Acetate

Drug Facts:

Active Ingredients:

Titanium Dioxide 8%

Zinc Oxide 3.8%

Purpose:

Sunscreen

Sunscreen

Uses:

Helps prevent sunburn. If used as directed with other sun protection measures (see directions), decreases the risk of skin cancer and early skin aging caused by the sun'

Warnings:

For external use only. Do not use on damaged or broken skin. Stop use and ask a doctor if rash occurs. When using this product, keep out of eyes. Rinse with water to remove.

KEEP OUT OF REACH OF CHILDREN

Keep out of the reach of children. If swallowed, get medical help or contact a Poison Control Center right away.

Directions:

Apply liberally 15 minutes before sun exposure.

- Reapply:
  - After 80 minutes of swimming or sweating
  - Immediately after towel drying
  - At least every 2 hours
- Children under 6 months: Ask a doctor

Sun Protection Measures: Spending time in the sun increases your risk of skin cancer and early skin aging. To decrease this risk, regularly use a sunscreen with a Broad Spectrum SPF value of 15 or higher and other sun protection measures including:

- Limit time in the sun, especially from 10:00 am - 2:00 pm
- Wear long-sleeved shirts, pants, hats, and sunglasses

Inactive Ingredients:

Alumina, Cyclohexasiloxane, Cyclopentasiloxane, Dimethicone, Dimethicone Crosspolymer, Dimethicone/Vinyl Dimethicone Crosspolymer, Dimethiconol, Iron Oxide (Cl 77491), Lauryl PEG/PPG-18/18 Methicone, Hydrogen Dimethicone, PEG-10 Dimethicone, Tetrahexyldecyl Ascorbate, Tocopheryl Acetate

Other Information:

- Protect this product from excessive heat and direct sun
- May stain some fabrics
- PA +++

Manufactured by Emme Diane™

Scottsdale, AZ - www.emmediane.com

Principal Display Panel – 53 g Bottle Label

EMME DIANE

TINTED
MINERAL
SUNSCREEN

BROAD SPECTRUM SPF 40
WATER RESISTANT
(80 MINUTES)

NET WT. 1.8 OZ (53 G)